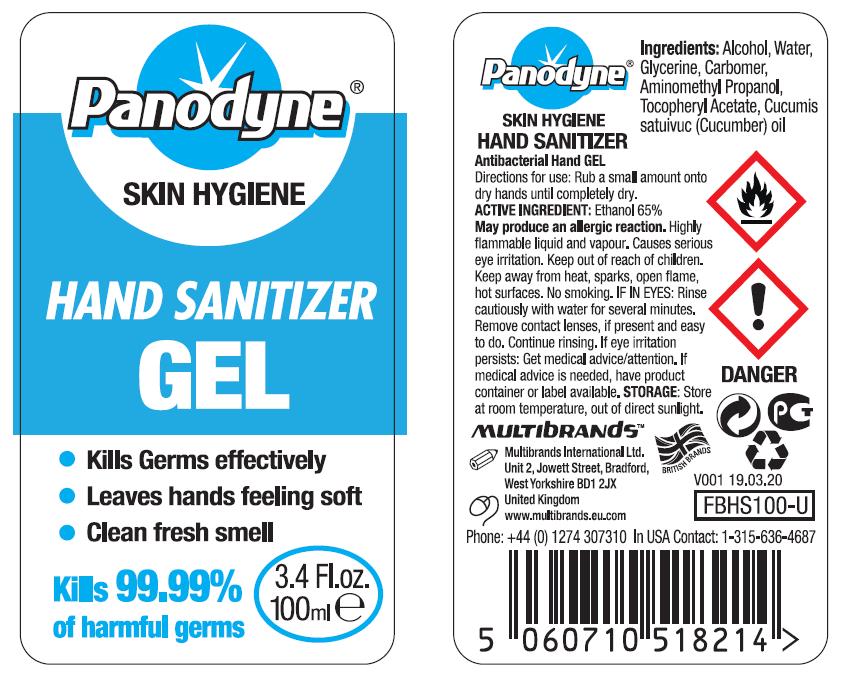 DRUG LABEL: Panodyne HAND SANITIZER 99.9% Protection
NDC: 73968-1013 | Form: GEL
Manufacturer: Multibrands International Limited
Category: otc | Type: HUMAN OTC DRUG LABEL
Date: 20200407

ACTIVE INGREDIENTS: ALCOHOL 70 mL/100 mL
INACTIVE INGREDIENTS: TROLAMINE 0.5 mL/100 mL; WATER 26 mL/100 mL; GLYCERIN 3 mL/100 mL; CARBOMER HOMOPOLYMER, UNSPECIFIED TYPE 0.5 mL/100 mL

MultiBrands, Hand Sanitizer, Gel, 70% Alcohol, 100mL

Active Ingredient(s)

Ethanol 65%

Purpose

Antiseptic, Hand Sanitizer

Use

Hand Sanitizer to help reduce bacteria that potentially can cause disease. For use when soap and water are not available.

Warnings

May producean allergic reaction. Flammable. For external use only. Keep away from heat, sparks, open flame, hot surfaces. Cause serious eye irritation. Keep out of reach of children. No smoking.

Do not use

- on children less than 2 months of age
- on open skin wounds

When using this product keep out of eyes, ears, and mouth.

In case of contact with eyes, rinse eyes thoroughly with water.

Stop use and ask a doctor if irritation or rash occurs. These may be signs of a serious condition.

Keep out of reach of children. If swallowed, get medical help or contact a Poison Control Center right away.

Directions

- Place enough product on hands to cover all surfaces. Rub hands together until dry.
- Supervise children under 6 years of age when using this product to avoid swallowing.

Other information

- Store at room temperature, out of direct sunlight

Inactive ingredients

Water, Glycerine, Carbomer, Aminomethyl Propanol, Tocopheryl Acetate, Cucumis satuivuc (Cucumber) oil.